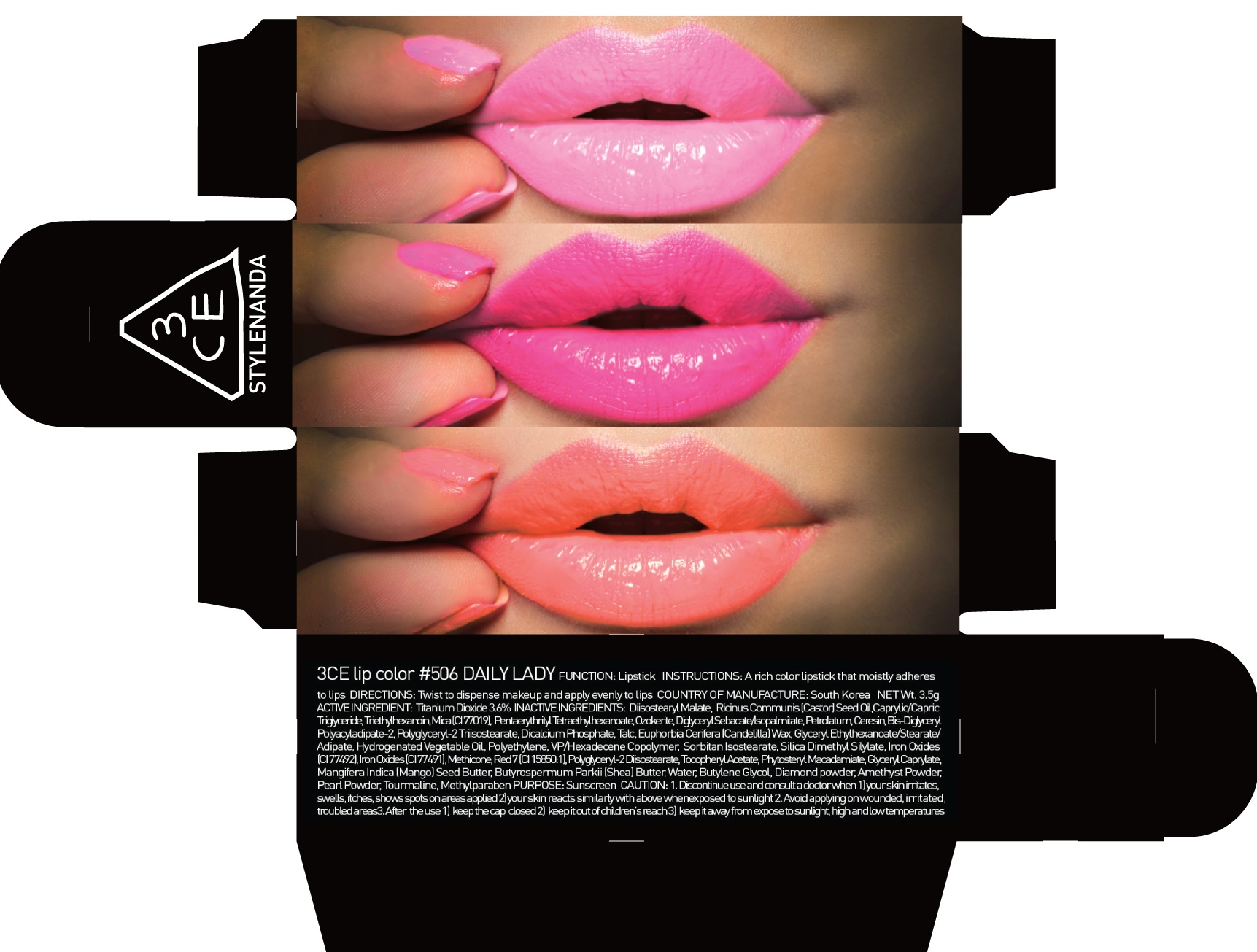 DRUG LABEL: 3CE LIP COLOR 506 DAILY LADY
NDC: 60764-075 | Form: LIPSTICK
Manufacturer: Nanda Co., Ltd
Category: otc | Type: HUMAN OTC DRUG LABEL
Date: 20161007

ACTIVE INGREDIENTS: Titanium Dioxide 0.12 g/3.5 g
INACTIVE INGREDIENTS: Diisostearyl Malate; Mica

ACTIVE INGREDIENT

Active Ingredient: Titanium Dioxide 3.6%

INACTIVE INGREDIENT

Inactive Ingredients: Diisostearyl Malate, Ricinus Communis (Castor) Seed Oil, Caprylic/Capric Triglyceride, Triethylhexanoin, Mica (CI 77019), Pentaerythrityl Tetraethylhexanoate, Ozokerite, Diglyceryl Sebacate/Isopalmitate, Petrolatum, Ceresin, Bis-Diglyceryl Polyacyladipate-2, Polyglyceryl-2 Triisostearate, Dicalcium Phosphate, Talc, Euphorbia Cerifera (Candelilla) Wax, Glyceryl Ethylhexanoate/Stearate/Adipate, Hydrogenated Vegetable Oil, Polyethylene, VP/Hexadecene Copolymer, Sorbitan Isostearate, Silica Dimethyl Silylate, Iron Oxides (CI 77492), Iron Oxides (CI 77491), Methicone, Red 7 (CI 15850:1), Polyglyceryl-2 Diisostearate, Tocopheryl Acetate, Phytosteryl Macadamiate, Glyceryl Caprylate, Mangifera Indica (Mango) Seed Butter, Butyrospermum Parkii (Shea) Butter, Water, Butylene Glycol, Diamond powder, Amethyst Powder, Pearl Powder, Tourmaline, Methylparaben

PURPOSE

Purpose: Sunscreen

CAUTION

CAUTION: 1. Discontinue use and consult a doctor when - your skin irritates, swells, itches, shows spots on areas applied - your skin reacts similarly with above when exposed to sunlight 2. Avoid applying on wounded, irritated, troubled areas 3. After the use - keep the cap closed - keep it out of children's reach - keep it away from expose to sunlight, high and low temperatures

DESCRIPTION

INSTRUCTIONS: A rich color lipstick that moistly adheres to lips.

Directions: Twist to dispense makeup and apply evenly to lips